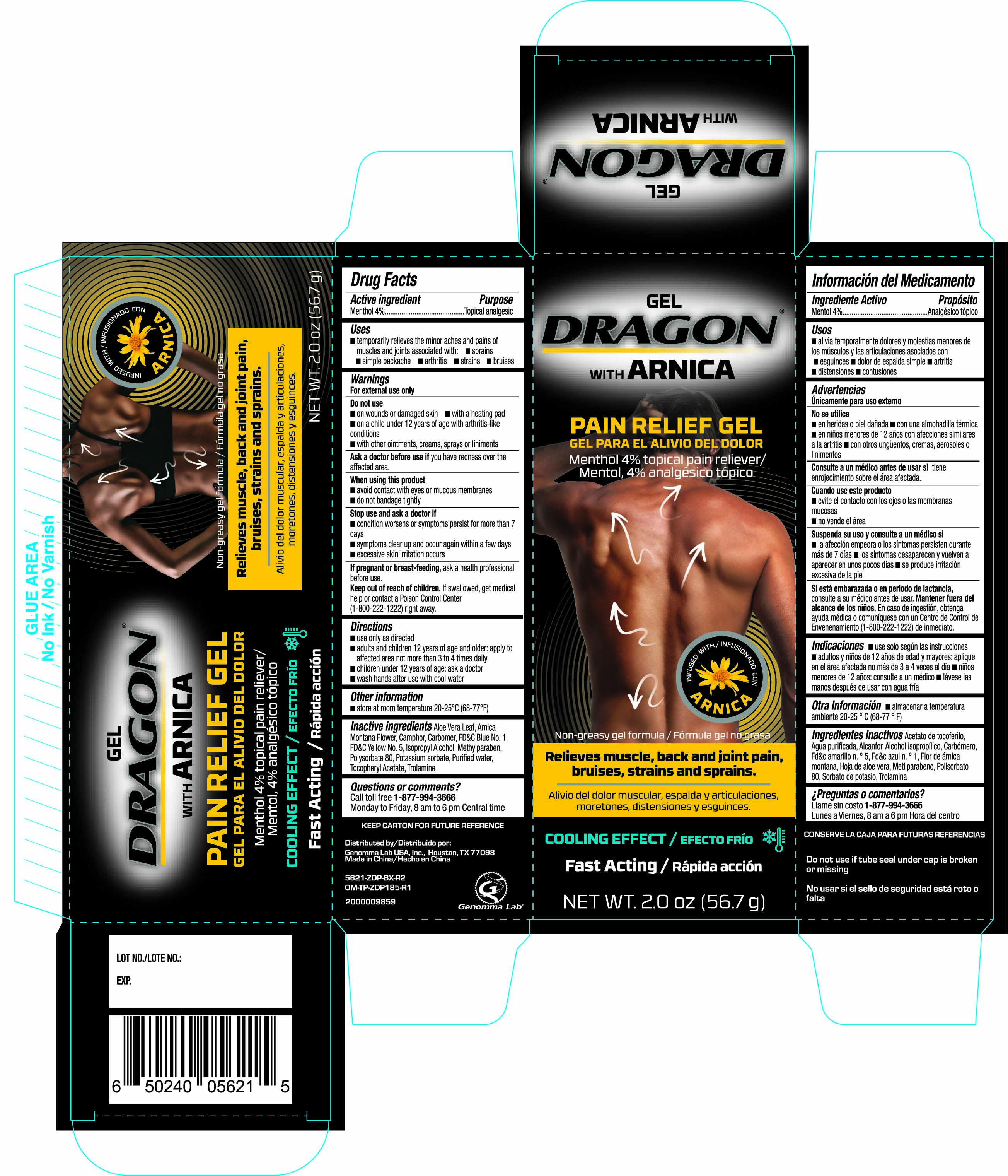 DRUG LABEL: Dragon with Arnical Pain Relief
NDC: 50066-621 | Form: GEL
Manufacturer: Genomma Lab USA Inc.
Category: otc | Type: HUMAN OTC DRUG LABEL
Date: 20251031

ACTIVE INGREDIENTS: MENTHOL 4 g/100 g
INACTIVE INGREDIENTS: ALOE VERA LEAF; ARNICA MONTANA FLOWER; CAMPHOR (SYNTHETIC); CARBOMER HOMOPOLYMER, UNSPECIFIED TYPE; ISOPROPYL ALCOHOL; FD&C BLUE NO. 1; WATER; FD&C YELLOW NO. 5; POLYSORBATE 80; POTASSIUM SORBATE; TROLAMINE; METHYLPARABEN

Dragon with Arnical Pain Relief Gel 2 oz 5621 ZDP

Active ingredient Purpose

Menthol 4%.......................................................Topical analgesic

Uses

- temporarily relieves the minor aches and pains of muscles and joints associated with:
- sprains
- simple backache
- arthirtis
- strains bruises

Warnings

For external use only

Do not use

- on wounds or damaged skin
- with a heating pad
- on a child under 12 years of age with arthritis-like conditions
- with other ointments, creams, sprays or liniments

Ask a doctor before use if you have redness over the affected area.

When using this product

- avoid contact with eyes or mucous membranes
- do not bandage tightly

Stop use and ask a doctor if

- condition worsens or symptoms persist for more than 7 days
- symptoms clear up and occur again within a few days
- excessive skin irritation occurs

PREGNANCY OR BREAST FEEDING

If pregnant or breast-feeding, ask a health professional before use.

Keep out of reach of children. If swallowed, get medical help or contact a Poison Control Center (1-800-222-1222) right away.

Directions

- use only as directed
- adults and children 12 years of age and older: apply to affected area not more than 3 to 4 times daily
- children under 12 years of age: ask a doctor
- wash hands after use with cool water

Other information

store at room temperature 20-25°C (68-77°F)

Inactive ingredients

Aloe Vera Leaf, Arnica Montana Flower, Camphor, Carbomer, FD&C Blue No. 1, FD&C Yellow No. 5, Isopropyl Alcohol, Methylparaben, Polysorbate 80, Potassium sorbate, Purified water, Tocopheryl Acetate, Trolamine

DOSAGE AND ADMINISTRATION

Distributed by:

Genomma Lab USA, Inc.

Houston, TX 77027

Made in China